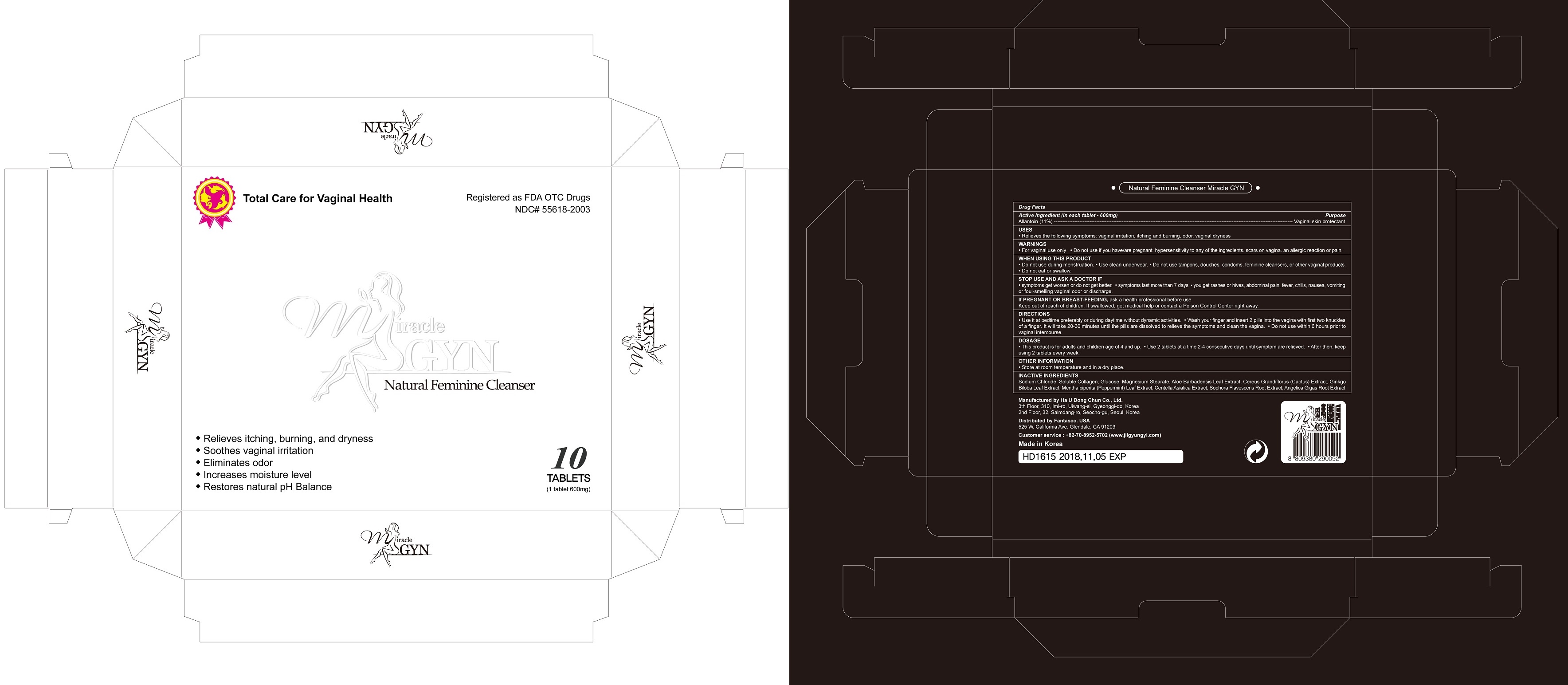 DRUG LABEL: Miracle GYN (10 Tablets)
NDC: 55618-2003 | Form: TABLET
Manufacturer: Haudongchun Co., Ltd.
Category: otc | Type: HUMAN OTC DRUG LABEL
Date: 20170324

ACTIVE INGREDIENTS: ALLANTOIN 0.11 1/600 mg
INACTIVE INGREDIENTS: Sodium Chloride; .ALPHA.-D-GLUCOPYRANOSE; MAGNESIUM STEARATE; ALOE VERA LEAF; GINKGO; MENTHA PIPERITA LEAF; CENTELLA ASIATICA; SOPHORA FLAVESCENS ROOT; ANGELICA GIGAS ROOT

Miracle GYN (10 tablets)

Active Ingredients

Allantoin (11%)

Purpose

Vaginal skin protectant

Keep out of reach of children. If swallowed, get medical help or contact a Poison Control right away. (1-800-222-1222)

Uses

 Relieves the following symptoms: vaginal irritation, itching and burning, odor, vaginal dryness

Warnings

 For vaginal use only
 Do not use if you have/are pregnant, hypersensitivity to any of the ingredients, scars on vagina, an allergic reaction or pain.

When using this product
 Do not use during menstruation.
 Use clean underwear.
 Do not use tampons, douches, condoms, feminine cleansers, or other vaginal products.
 Do not eat or swallow.

Stop use and ask a doctor if
 Symptoms get worsen or do not get better.
 Symptoms last more than 7 days
 You get rashes or hives, abdominal pain, fever, chills, nausea, vomiting or foul-smelling vaginal odor or discharge.

If pregnant or breast-feeding, ask a health professional before use.

Directions & Dosage

 Use it at bedtime preferably or during daytime without dynamic activites.
 Wash your finger and insert 2 pills into the vagina with first two knuckles of a finger. It will take 20-30 minutes until the pills are dissolved to relieve the symptoms and clean the vagina.
 Do not use within 6 hours prior to vaginal intercourse.

 This product is for adults and children age of 4 and up.
 Use 2 tablets at a time 2-4 consecutive days until symptoms are relieved.
 After then, keep using 2 tablets every week

Other Information
 Store at cool temperature and dry place

Inactive Ingredients

Sodium Chloride, Soluble Collagen, Glucose, Magnesium Stearate, Aloe Barbadensis Leaf Extract, Cereus Grandiflorus (Cactus) Extract, Ginkgo Biloba Leaf Extract, Mentha Piperita (Peppermint) Leaf Extract, Centella Asiatica Extract, Sophora Flavescens Root Extract, Angelica Gigas Root Extract